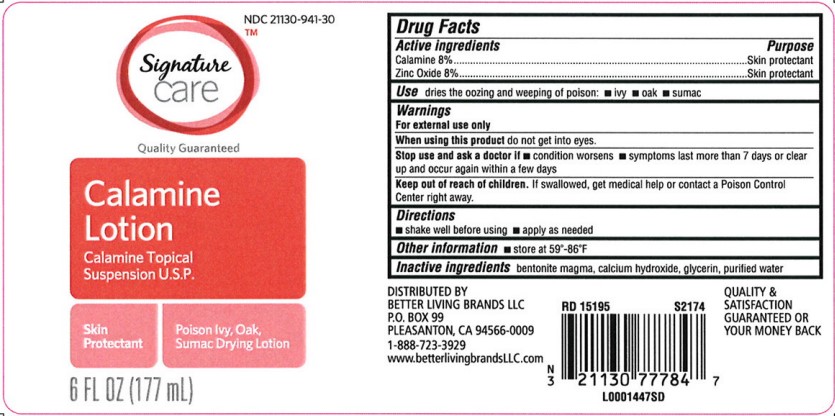 DRUG LABEL: Calamine
NDC: 21130-941 | Form: LOTION
Manufacturer: Better Living Brands, LLC
Category: otc | Type: HUMAN OTC DRUG LABEL
Date: 20260223

ACTIVE INGREDIENTS: FERRIC OXIDE RED 80 mg/1 mL; ZINC OXIDE 80 mg/1 mL
INACTIVE INGREDIENTS: BENTONITE; CALCIUM HYDROXIDE; GLYCERIN; WATER

Signature Care 063.001/063AA
Calamine Lotion

Active ingredents

Calamine 8%
Zinc oxide 8%

Purpose

Skin Protectant

Use

dries the oozing and weeping of poison:

- ivy
- oak
- sumac

Warnings

For external use only

When using this product

Do not get into eyes

Stop use and ask a doctor if

- condition worsens
- symptoms last more than 7 days or clear up and occur again within a few days

Keep out of reach of children

If swallowed, get medical help or contact a Poison Control Center right away

Directions

- shake well before using
- apply as needed

Other information

store at 59⁰ - 86⁰ F

Inactive ingredients

bentonite magma, calcium hydroxide, glycerin, purified water

Adverse Reaction

DISTRIBUTED BY BETTER LIVING BRANDS LLC

P.O. BOX 99, PLEASANTON, CA 94566-0009

1-888-723-3929 www.betterlivingbrandsLLC.com

QUALITY & SATISFACTION GUARANTEED OR YOUR MONEY BACK

principal display panel

NDC 21130-941-30

Signature Care™

Quality Guaranteed

Calamine Lotion

Calamine Topical Suspension U.S.P.

Skin Protectant

Poison Ivy, Oak, Sumac Drying Lotion

6 FL OZ (177 mL)